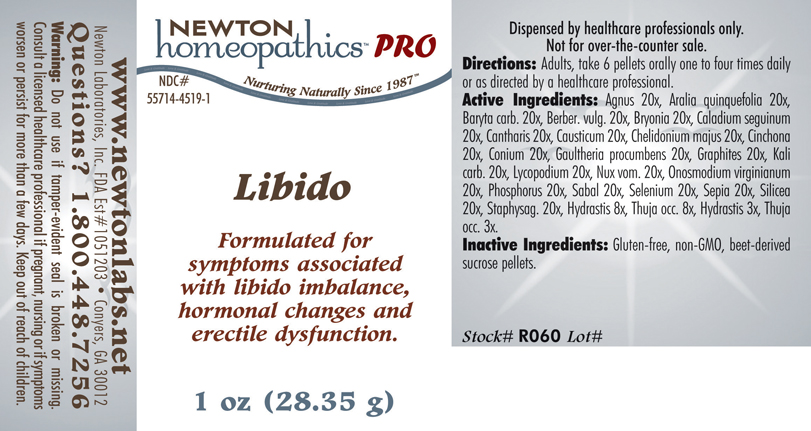 DRUG LABEL: Libido 
NDC: 55714-4519 | Form: PELLET
Manufacturer: Newton Laboratories, Inc.
Category: homeopathic | Type: HUMAN PRESCRIPTION DRUG LABEL
Date: 20110601

ACTIVE INGREDIENTS: Chaste Tree 20 [hp_X]/1 g; American Ginseng 20 [hp_X]/1 g; Barium Carbonate 20 [hp_X]/1 g; Berberis Vulgaris Root Bark 20 [hp_X]/1 g; Bryonia Alba Root 20 [hp_X]/1 g; Dieffenbachia Seguine 20 [hp_X]/1 g; Lytta Vesicatoria 20 [hp_X]/1 g; Causticum 20 [hp_X]/1 g; Chelidonium Majus 20 [hp_X]/1 g; Cinchona Officinalis Bark 20 [hp_X]/1 g; Conium Maculatum Flowering Top 20 [hp_X]/1 g; Gaultheria Procumbens Top 20 [hp_X]/1 g; Graphite 20 [hp_X]/1 g; Potassium Carbonate 20 [hp_X]/1 g; Lycopodium Clavatum Spore 20 [hp_X]/1 g; Strychnos Nux-vomica Seed 20 [hp_X]/1 g; Onosmodium Virginianum Root 20 [hp_X]/1 g; Phosphorus 20 [hp_X]/1 g; Saw Palmetto 20 [hp_X]/1 g; Selenium 20 [hp_X]/1 g; Sepia Officinalis Juice 20 [hp_X]/1 g; Silicon Dioxide 20 [hp_X]/1 g; Delphinium Staphisagria Seed 20 [hp_X]/1 g; Goldenseal 8 [hp_X]/1 g; Thuja Occidentalis Leafy Twig 8 [hp_X]/1 g
INACTIVE INGREDIENTS: Sucrose

Libido

INDICATIONS & USAGE SECTION

Libido Formulated for symptoms associated with libido imbalance, hormonal changes and erectile dysfunction.

DOSAGE & ADMINISTRATION SECTION

Directions: Adults, take 6 pellets orally one to four times daily or as directed by a healthcare professional.

ACTIVE INGREDIENT SECTION

Agnus 20x, Aralia quinquefolia 20x, Baryta carb. 20x, Berber. vulg. 20x, Bryonia 20x, Caladium seguinum 20x, Cantharis 20x, Causticum 20x, Chelidonium majus 20x, Cinchona 20x, Conium 20x, Gaultheria procumbens 20x, Graphites 20x, Kali carb. 20x, Lycopodium 20x, Nux vom. 20x, Onosmodium virginianum 20x, Phosphorus 20x, Sabal 20x, Selenium 20x, Sepia 20x, Silicea 20x, Staphysag. 20x, Hydrastis 8x, Thuja occ. 8x, Hydrastis 3x, Thuja occ. 3x.

PURPOSE SECTION

Formulated for symptoms associated with libido imbalance, hormonal changes and erectile dysfunction.

INACTIVE INGREDIENT SECTION

Inactive Ingredients: Gluten-free, non-GMO, beet-derived sucrose pellets.

QUESTIONS? SECTION

www.newtonlabs.net Newton Laboratories, Inc. FDA Est # 1051203 - Conyers, GA 30012
Questions? 1.800.448.7256

WARNINGS SECTION

Warning: Do not use if tamper - evident seal is broken or missing. Consult a licensed healthcare professional if pregnant, nursing or if symptoms worsen or persist for more than a few days. Keep out of reach of children.

PREGNANCY OR BREAST FEEDING SECTION

Consult a licensed healthcare professional if pregnant, nursing or if symptoms worsen or persist for more than a few days.

KEEP OUT OF REACH OF CHILDREN SECTION

Keep out of reach of children.